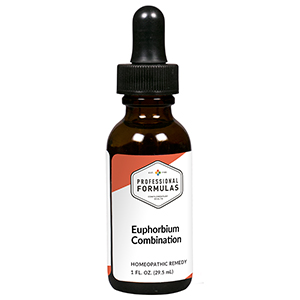 DRUG LABEL: Euphorbium Combination
NDC: 63083-9255 | Form: LIQUID
Manufacturer: Professional Complementary Health Formulas
Category: homeopathic | Type: HUMAN OTC DRUG LABEL
Date: 20190815

ACTIVE INGREDIENTS: PLANTAGO MAJOR WHOLE 3 [hp_X]/29.5 mL; PULSATILLA MONTANA WHOLE 4 [hp_X]/29.5 mL; EUPHORBIA RESINIFERA RESIN 6 [hp_X]/29.5 mL; LUFFA OPERCULATA FRUIT 6 [hp_X]/29.5 mL; MERCURIC IODIDE 8 [hp_X]/29.5 mL; SUS SCROFA NASAL MUCOSA 8 [hp_X]/29.5 mL; SILVER NITRATE 10 [hp_X]/29.5 mL; CALCIUM SULFIDE 10 [hp_X]/29.5 mL; SINUSITISINUM 12 [hp_X]/29.5 mL; DIPHTHERIAL RESPIRATORY PSEUDOMEMBRANE HUMAN 30 [hp_X]/29.5 mL
INACTIVE INGREDIENTS: ALCOHOL; WATER

R255

ACTIVE INGREDIENTS

Plantago major 3X
Pulsatilla 4X
Euphorbium officinarum 6X
Luffa operculata 6X
Mercurius iodatus ruber 8X
Mucosa nasalis 8X
Argentum nitricum 10X
Hepar sulphuris calcareum 10X
Sinusitis 12X
Diphtherinum 30X

QUESTIONS

Professional Formulas

PO Box 2034 Lake Oswego, OR 97035

INDICATIONS

For the temporary relief of runny nose, nasal congestion, headache, or mild facial or ear pain due to a cold, hay fever, or other upper respiratory allergies.*

PURPOSE

*Claims based on traditional homeopathic practice, not accepted medical evidence. Not FDA evaluated.

WARNINGS

If symptoms do not improve or are accompanied by a fever, consult a doctor. Keep out of the reach of children. In case of overdose, get medical help or contact a poison control center right away. If pregnant or breastfeeding, ask a healthcare professional before use.

Keep out of the reach of children.

PREGNANCY OR BREAST FEEDING

If pregnant or breastfeeding, ask a healthcare professional before use.

DIRECTIONS

Place drops under tongue 30 minutes before/after meals. Adults and children 12 years and over: Take 10 drops up to 3 times per day. Consult a physician for use in children under 12 years of age.

OTHER INFORMATION

Tamper resistant. If seal is broken, do not use. After opening, close container tightly and store at room temperature away from heat.

INACTIVE INGREDIENTS

40% ethanol, purified water.

LABEL

Est 1985

Professional Formulas

Complementary Health

Euphorbium Combination

Homeopathic Remedy

1 FL. OZ. (29.5 mL)